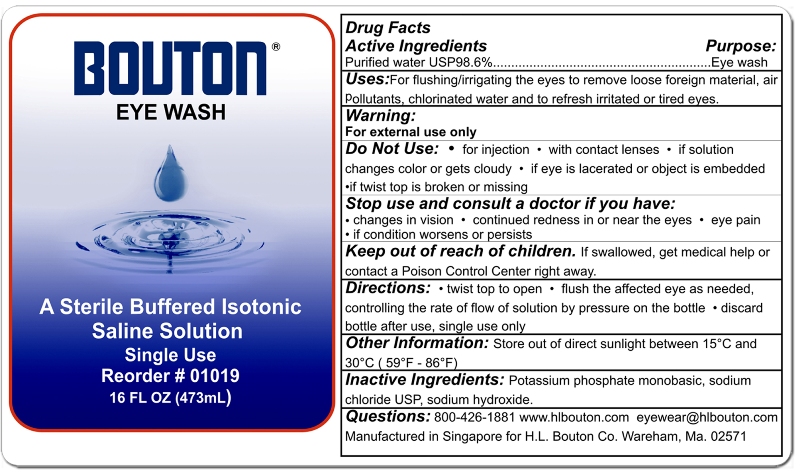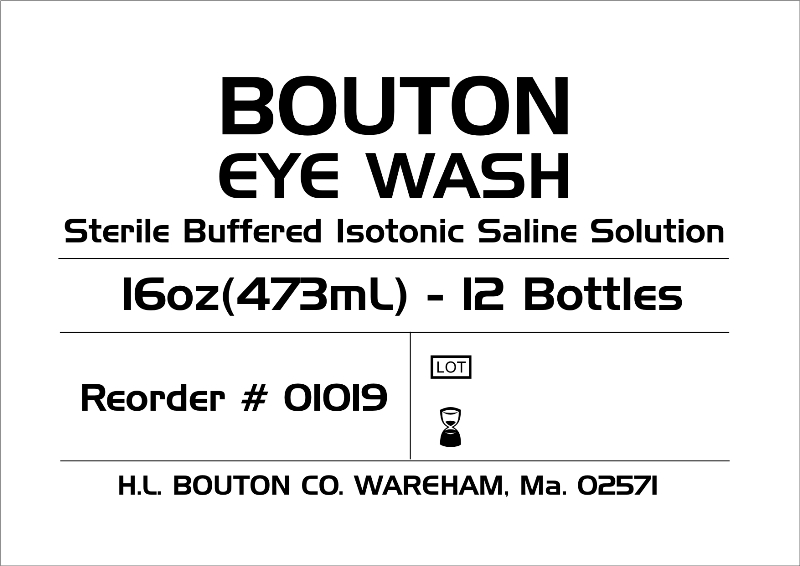 DRUG LABEL: Bouton 
NDC: 68276-004 | Form: RINSE
Manufacturer: Aaxis Pacific
Category: otc | Type: HUMAN OTC DRUG LABEL
Date: 20100705

ACTIVE INGREDIENTS: Water 98.6 mL/100 mL

Active Ingredients Purpose:

Purified water USP98.6%............................................Eye Wash

Purpose:

Eye Wash

INDICATIONS AND USAGE

Uses: For flushing/irrigating the eyes to remove loose foreign material, air pollutants, chlorinated water and to refresh irritated or tired eyes.

Warning:

For external use only

Do Not Use:

- for injection
- with contact lenses
- if solution changes color or gets cloudy
- if eye is lacerated or object is embedded
- if twist top is broken or missing

Stop use and consult a doctor if you have:

- changes in vision
- continued redness in or near the eyes
- eye pain
- if condition worsens or persists

Keep out of reach of children.

If swallowed, get medical help or contact a Poison Control Center right away.

Directions:

- twist top to open
- flush the affected eye as needed, controlling the rate of flow of solution by pressure on the bottle
- discard bottle after use, single use only

Other Information:

Store out of direct sunlight between 15 degrees C and 30 degrees C (59 degrees F - 86 degrees F)

Inactive Ingredients:

Potassium phosphate monobasic, sodium chloride USP, sodium hydroxide.

Questions:

800-426-1881 www.hlbouton.com eyewear@hlbouton.com

Manufactured in Singapore for H.L. Bouton Co. Wareham, Ma. 02571